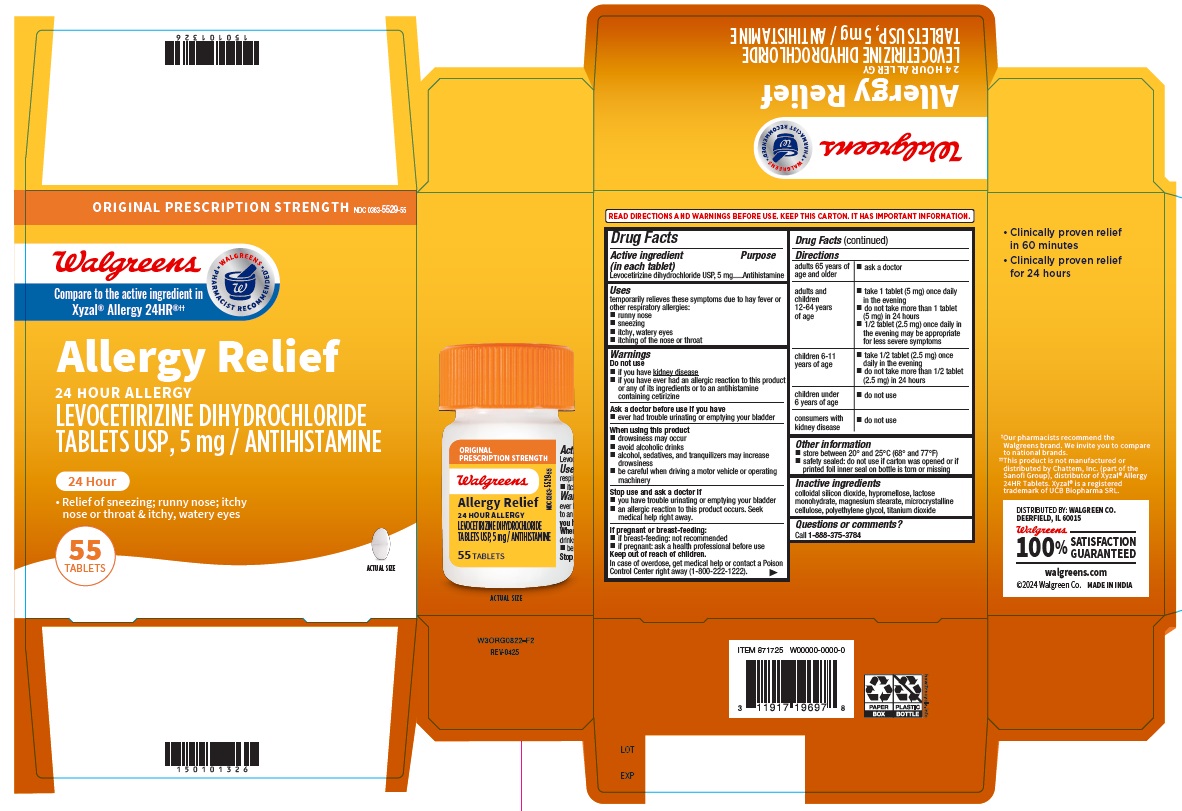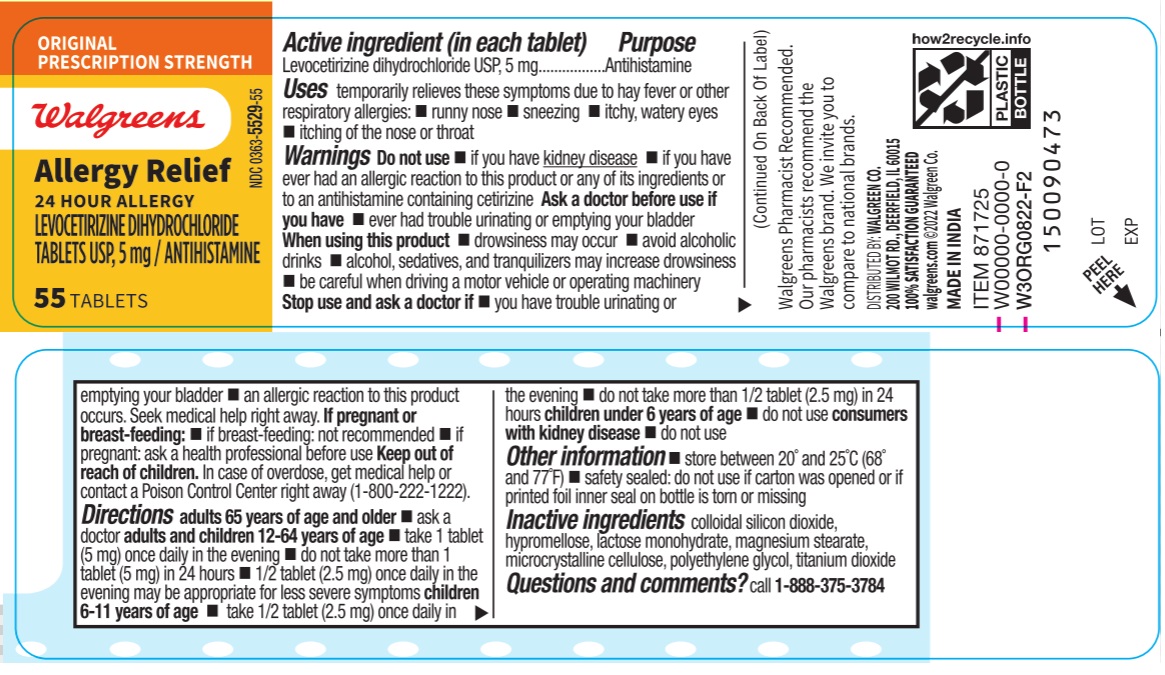 DRUG LABEL: levocetirizine dihydrochloride
NDC: 0363-5529 | Form: TABLET, COATED
Manufacturer: Walgreens Company
Category: otc | Type: HUMAN OTC DRUG LABEL
Date: 20260120

ACTIVE INGREDIENTS: levocetirizine dihydrochloride 5 mg/1 1
INACTIVE INGREDIENTS: CELLULOSE, MICROCRYSTALLINE; LACTOSE MONOHYDRATE; SILICON DIOXIDE; MAGNESIUM STEARATE; HYPROMELLOSES; TITANIUM DIOXIDE; Polyethylene Glycol, Unspecified

Drug Facts

Active ingredient (in each tablet)

Levocetirizine dihydrochloride USP, 5 mg

Purpose

Antihistamine

Uses

temporarily relieves these symptoms due to hay fever or other respiratory allergies:

- runny nose
- sneezing
- itchy, watery eyes
- itching of the nose or throat

Warnings

Do not use

- if you have kidney disease
- if you have ever had an allergic reaction to this product or any of its ingredients or to an antihistamine containing cetirizine

Ask a doctor before use if you have

- ever had trouble urinating or emptying your bladder

When using this product

- drowsiness may occur
- avoid alcoholic drinks
- alcohol, sedatives, and tranquilizers may increase drowsiness
- be careful when driving a motor vehicle or operating machinery

Stop use and ask doctor if

- you have trouble urinating or emptying your bladder
- an allergic reaction to this product occurs. Seek medical help right away.

If pregnant or breast-feeding:

- if breast-feding: not recommended
- if pregnant: ask a health professional before use

Keep out of reach of children

In case of overdose, get medical help or contact a Poison Control Center right away (1-800-222-1222).

Directions

adults 65 years of age and older | - ask a doctor
adults and children 12-64 years of age | - take 1 tablet (5 mg) once daily in the evening - do not take more than 1 tablet (5 mg) in 24 hours - 1/2 tablet (2.5 mg) once daily in the evening may be appropriate for less severe symptoms
children 6-11 years of age | - take 1/2 tablet (2.5 mg) once daily in the evening - do not take more than 1/2 tablet (2.5 mg) in 24 hours
children under 6 years of age | - do not use
consumers with kidney disease | - do not use

Other information

- store between 20° and 25°C (68° and 77°F)
- (bottles only) safety sealed: do not use if carton was opened or if printed foil inner seal on bottle is torn or missing
- (blister only) safety sealed: do not use if seal is broken or if individual blister unit is open or torn

Inactive ingredients

colloidal silicon dioxide, hypromellose, lactose monohydrate, magnesium stearate, microcrystalline cellulose, polyethylene glycol, titanium dioxide

Questions or comments?

Call 1-888-375-3784

Carton Label

ORIGINAL PRESCRIPTION STRENGTH
Compare to Xyzal®Allergy 24HR active ingredient‡‡

0363-5529-55

NEW Well at Walgreens
WALGREENS PHARMACIST RECOMMENDED‡

ORIGINAL
PRESCRIPTION
STRENGTH

Levocetirizine
24-Hour Allergy

Levocetirizine Dihydrochloride
Tablets, 5 mg / Antihistamine

Relief of:

- Sneezing
- Runny nose
- Itchy nose or throat
- Itchy, watery eyes

24 HOUR

55 TABLETS

Bottle Label

Well at Walgreens

NDC 0363-5529-55

ORIGINAL
PRESCRIPTION STRENGTH

Levocetirizine
24-Hour Allergy

Levocetirizine Dihydrochloride
Tablets, 5 mg / Antihistamine

55 TABLETS